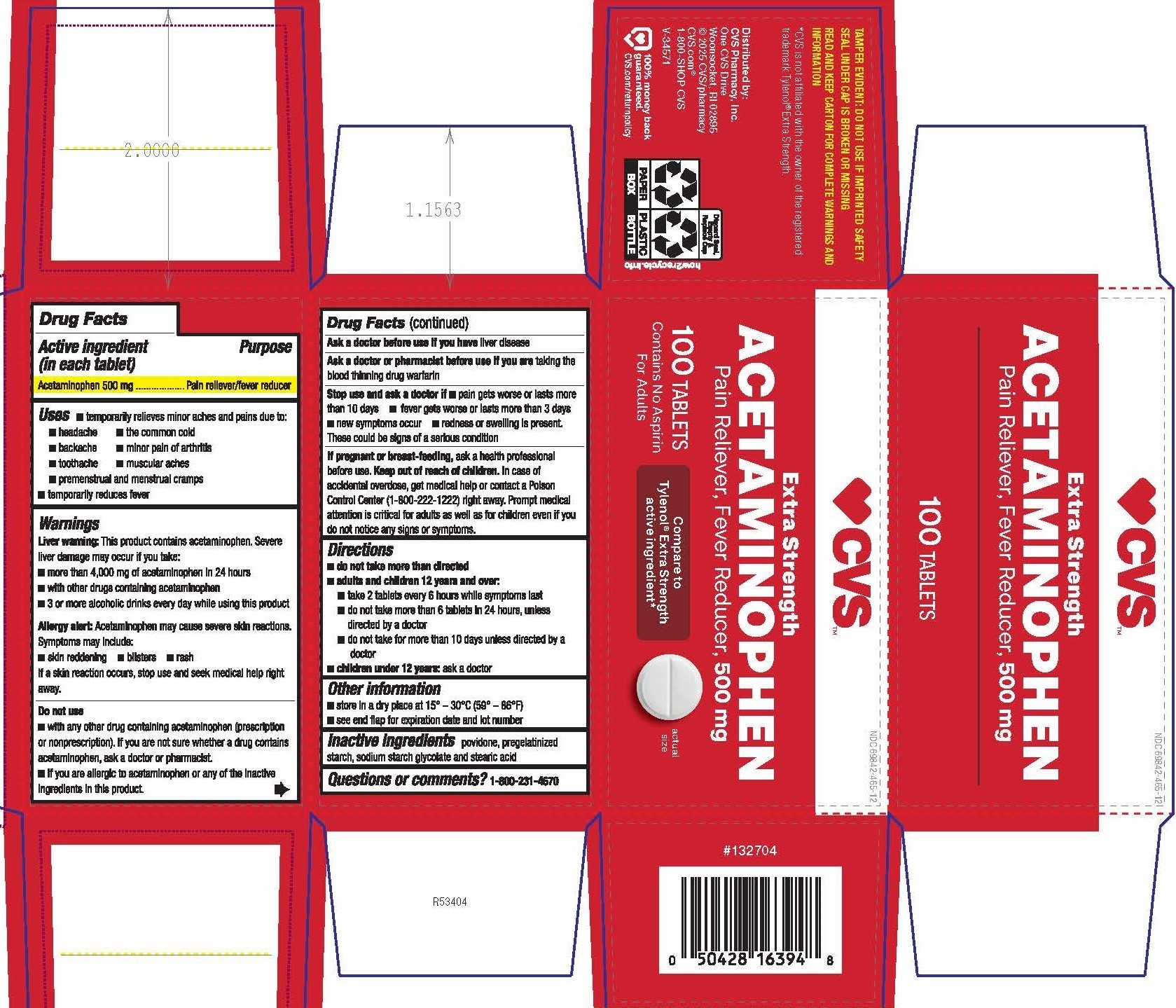 DRUG LABEL: Acetaminophen
NDC: 69842-465 | Form: TABLET
Manufacturer: CVS Pharmacy, Inc.
Category: otc | Type: HUMAN OTC DRUG LABEL
Date: 20250610

ACTIVE INGREDIENTS: ACETAMINOPHEN 500 mg/1 1
INACTIVE INGREDIENTS: STARCH, PREGELATINIZED CORN; STEARIC ACID; POVIDONE; SODIUM STARCH GLYCOLATE TYPE A POTATO

0546-CVS

Drug Facts

Active ingredient (in each tablet)

Acetaminophen 500 mg

Purpose

Pain reliever/fever reducer

Uses

- temporarily relieves minor aches and pains due to:
- headache
- the common cold
- backache
- minor pain of arthritis
- toothache
- muscular aches
- premenstrual and menstrual cramps
- temporarily reduces fever

Warnings

Liver warning: This product contains acetaminophen. Severe liver damage may occur if you take:

- more than 4,000 mg of acetaminophen in 24 hours
- with other drugs containing acetaminophen
- 3 or more alcoholic drinks every day while using this product

Allergy alert: Acetaminophen may cause severe skin reactions.

Symptoms may include:

- skin reddening
- blisters
- rash

If a skin reaction occurs, stop use and seek medical help right away.

Do not use

- with any other drug containing acetaminophen (prescription or nonprescription). If you are not sure whether a drug contains

acetaminophen, ask a doctor or pharmacist.

- if you are allergic to acetaminophen or any of the inactive ingredients in this product.

Ask a doctor before use if you have

liver disease

Ask a doctor or pharmacist before use if you are

taking the blood thinning drug warfarin

Stop use and ask a doctor if

■ pain gets worse or lasts more than 10 days

■ fever gets worse or lasts more than 3 days

■ new symptoms occur

■ redness or swelling is present.

These could be signs of a serious condition

If pregnant or breast-feeding,

ask a health professional before use.

OVERDOSAGE

In case of accidental overdose, get medical help or contact a Poison Control Center (1-800-222-1222) right away. Prompt medical

attention is critical for adults as well as for children even if you do not notice any signs or symptoms.

Directions

■ do not take more than directed

■ adults and children 12 years and over:

■ take 2 tablets every 6 hours while symptoms last

■ do not take more than 6 tablets in 24 hours, unless directed by a doctor

■ do not take for more than 10 days unless directed by a doctor

■ children under 12 years: ask a doctor

Other information

■ store in a dry place at 15°-30°C (59°-86°F)

■ see end flap for expiration date and lot number

Inactive ingredients

povidone, pregelatinized starch, sodium starch glycolate and stearic acid

Questions or comments?

1-800-231-4670

TAMPER EVIDENT: DO NOT USE IF IMPRINTED SAFETY SEAL UNDER CAP IS BROKEN OR MISSING

READ AND KEEP CARTON FOR COMPLETE WARNINGS AND INFORMATION

*CVS is not affiliated with the owner of the registered trademark Tylenol® Extra Strength.

Distributed by: CVS Pharmacy, Inc.

One CVS Drive

Woonsocket, RI 02895

© 2025 CVS/pharmacy CVS.com®

1-800-SHOP CVS V-34571

PACKAGE LABEL

CVS

NDC 69842-465-12

Extra Strength

ACETAMINOPHEN

Pain Reliever, Fever Reducer, 500 mg

Compare to Tylenol® Extra Strength active ingredient*

100 TABLETS

Contains No Aspirin

For Adults